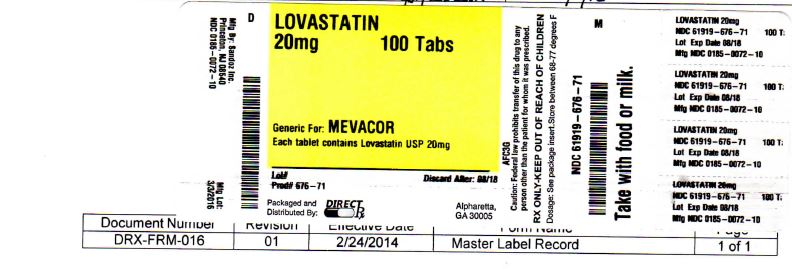 DRUG LABEL: LOVASTATIN
NDC: 61919-676 | Form: TABLET
Manufacturer: DIRECT RX
Category: prescription | Type: HUMAN PRESCRIPTION DRUG LABEL
Date: 20200120

ACTIVE INGREDIENTS: LOVASTATIN 20 mg/1 1
INACTIVE INGREDIENTS: BUTYLATED HYDROXYANISOLE; FD&C BLUE NO. 2; LACTOSE MONOHYDRATE; CELLULOSE, MICROCRYSTALLINE; MAGNESIUM STEARATE; STARCH, CORN

LOVASTATIN 20mg

DESCRIPTION

Lovastatin is a cholesterol lowering agent isolated from a strain of Aspergillus terreus. After oral ingestion, lovastatin, which is an inactive lactone, is hydrolyzed to the corresponding ß-hydroxyacid form. This is a principal metabolite and an inhibitor of 3-hydroxy-3-methylglutaryl-coenzyme A (HMG-CoA) reductase. This enzyme catalyzes the conversion of HMG-CoA to mevalonate, which is an early and rate limiting step in the biosynthesis of cholesterol.

Lovastatin is [1S-[1 α(R*),3 α,7ß,8ß(2S*,4S*), 8aß]]-1,2,3,7,8,8a-hexahydro-3,7-dimethyl-8-[2-(tetrahydro-4-hydroxy-6-oxo-2H-pyran-2-yl)ethyl]-1-naphthalenyl 2-methylbutanoate. The empirical formula of lovastatin is C24H3605 and its molecular weight is 404.55. Its structural formula is:

[Chemical Structure]

Lovastatin is a white, nonhygroscopic crystalline powder that is insoluble in water and sparingly soluble in ethanol, methanol, and acetonitrile.

Lovastatin Tablets USP are supplied as 10 mg, 20 mg and 40 mg tablets for oral administration. In addition to the active ingredient lovastatin, each tablet contains the following inactive ingredients: lactose monohydrate, magnesium stearate, microcrystalline cellulose and corn starch. Butylated hydroxyanisole (BHA) is added as a preservative. In addition the 10 mg tablets also contain red iron oxide and yellow iron oxide; the 20 mg tablets also contain FD&C blue No. 2; and the 40 mg tablets also contain D&C yellow No. 10 and FD&C blue No. 2.

CLINICAL PHARMACOLOGY I

The involvement of low-density lipoprotein cholesterol (LDL-C) in atherogenesis has been well-documented in clinical and pathological studies, as well as in many animal experiments. Epidemiological and clinical studies have established that high LDL-C and low high-density lipoprotein cholesterol (HDL-C) are both associated with coronary heart disease. However, the risk of developing coronary heart disease is continuous and graded over the range of cholesterol levels and many coronary events do occur in patients with total cholesterol (total-C) and LDL-C in the lower end of this range.

Lovastatin has been shown to reduce elevated LDL-C concentrations. LDL is formed from very low-density lipoprotein (VLDL) and is catabolized predominantly by the high affinity LDL receptor. The mechanism of the LDL-lowering effect of lovastatin may involve both reduction of VLDL-C concentration, and induction of the LDL receptor, leading to reduced production and/or increased catabolism of LDL-C. Apolipoprotein B also falls during treatment with lovastatin.

Lovastatin is a specific inhibitor of HMG-CoA reductase, the enzyme which catalyzes the conversion of HMG-CoA to mevalonate. The conversion of HMG-CoA to mevalonate is an early step in the biosynthetic pathway for cholesterol.

Pharmacokinetics

Lovastatin is a lactone which is readily hydrolyzed in vivo to the corresponding ß-hydroxyacid, a strong inhibitor of HMG-CoA reductase. Inhibition of HMG-CoA reductase is the basis for an assay in pharmacokinetic studies of the ß-hydroxyacid metabolites (active inhibitors) and, following base hydrolysis, active plus latent inhibitors (total inhibitors) in plasma following administration of lovastatin.

Following an oral dose of 14C-labeled lovastatin in man, 10% of the dose was excreted in urine and 83% in feces. The latter represents absorbed drug equivalents excreted in bile, as well as any unabsorbed drug. Plasma concentrations of total radioactivity (lovastatin plus 14C-metabolites) peaked at 2 hours and declined rapidly to about 10% of peak by 24 hours postdose. Absorption of lovastatin, estimated relative to an intravenous reference dose, in each of four animal species tested, averaged about 30% of an oral dose. In animal studies, after oral dosing, lovastatin had high selectivity for the liver, where it achieved substantially higher concentrations than in non-target tissues. Lovastatin undergoes extensive first-pass extraction in the liver, its primary site of action, with subsequent excretion of drug equivalents in the bile. As a consequence of extensive hepatic extraction of lovastatin, the availability of drug to the general circulation is low and variable. In a single dose study in four hypercholesterolemic patients, it was estimated that less than 5% of an oral dose of lovastatin reaches the general circulation as active inhibitors. Following administration of lovastatin tablets the coefficient of variation, based on between-subject variability, was approximately 40% for the area under the curve (AUC) of total inhibitory activity in the general circulation.

Both lovastatin and its ß-hydroxyacid metabolite are highly bound (>95%) to human plasma proteins. Animal studies demonstrated that lovastatin crosses the blood-brain and placental barriers.

The major active metabolites present in human plasma are the ß-hydroxyacid of lovastatin, its 6'-hydroxy derivative, and two additional metabolites. Peak plasma concentrations of both active and total inhibitors were attained within 2 to 4 hours of dose administration. While the recommended therapeutic dose range is 10 mg/day to 80 mg/day, linearity of inhibitory activity in the general circulation was established by a single dose study employing lovastatin tablet dosages from 60 mg to as high as 120 mg. With a once-a- day dosing regimen, plasma concentrations of total inhibitors over a dosing interval achieved a steady state between the second and third days of therapy and were about 1.5 times those following a single dose. When lovastatin was given under fasting conditions, plasma concentrations of total inhibitors were on average about two-thirds those found when lovastatin was administered immediately after a standard test meal.

In a study of patients with severe renal insufficiency (creatinine clearance 10 mL/min to 30 mL/min), the plasma concentrations of total inhibitors after a single dose of lovastatin were approximately two-fold higher than those in healthy volunteers.

In a study including 16 elderly patients between 70 to 78 years of age who received lovastatin 80 mg/day, the mean plasma level of HMG-CoA reductase inhibitory activity was increased approximately 45% compared with 18 patients between 18 to 30 years of age (see PRECAUTIONS, Geriatric Use).

Although the mechanism is not fully understood, cyclosporine has been shown to increase the AUC of HMG-CoA reductase inhibitors. The increase in AUC for lovastatin and lovastatin acid is presumably due, in part, to inhibition of CYP3A4.

The risk of myopathy is increased by high levels of HMG-CoA reductase inhibitory activity in plasma. Strong inhibitors of CYP3A4 can raise the plasma levels of HMG-CoA reductase inhibitory activity and increase the risk of myopathy (see WARNINGS, Myopathy/Rhabdomyolysisand PRECAUTIONS, Drug Interactions).

Lovastatin is a substrate for cytochrome P450 isoform 3A4 (CYP3A4) (see PRECAUTIONS, Drug Interactions). Grapefruit juice contains one or more components that inhibit CYP3A4 and can increase the plasma concentrations of drugs metabolized by CYP3A4. In one study1, 10 subjects consumed 200 mL of double-strength grapefruit juice (one can of frozen concentrate diluted with one rather than 3 cans of water) three times daily for 2 days and an additional 200 mL double-strength grapefruit juice together with and 30 and 90 minutes following a single dose of 80 mg lovastatin on the third day. This regimen of grapefruit juice resulted in a mean increase in the serum concentration of lovastatin and its ß-hydroxyacid metabolite (as measured by the area under the concentration-time curve) of 15-fold and 5-fold, respectively [as measured using a chemical assay - high performance liquid chromatography]. In a second study, 15 subjects consumed one 8 oz glass of single-strength grapefruit juice (one can of frozen concentrate diluted with 3 cans of water) with breakfast for 3 consecutive days and a single dose of 40 mg lovastatin in the evening of the third day. This regimen of grapefruit juice resulted in a mean increase in the plasma concentration (as measured by the area under the concentration-time curve) of active and total HMG-CoA reductase inhibitory activity [using an enzyme inhibition assay both before (for active inhibitors) and after (for total inhibitors) base hydrolysis] of 1.34-fold and 1.36-fold, respectively, and of lovastatin and its ß-hydroxyacid metabolite [measured using a chemical assay - liquid chromatography/tandem mass spectrometry - different from that used in the first1 study] of 1.94-fold and 1.57-fold, respectively. The effect of amounts of grapefruit juice between those used in these two studies on lovastatin pharmacokinetics has not been studied.

Table 1: The Effect of Other Drugs on Lovastatin Exposure When Both Were Co-Administered

*
Results based on a chemical assay.
†
Lovastatin acid refers to the β-hydroxyacid of lovastatin.
‡
The mean total AUC of lovastatin without itraconazole phase could not be determined accurately. Results could be representative of strong CYP3A4 inhibitors such as ketoconazole, posaconazole, clarithromycin, telithromycin, HIV protease inhibitors, and nefazodone.
§
Estimated minimum change.
¶
The effect of amounts of grapefruit juice between those used in these two studies on lovastatin pharmacokinetics has not been studied.
#
Double-strength: one can of frozen concentrate diluted with one can of water. Grapefruit juice was administered TID for 2 days, and 200 mL together with single dose lovastatin and 30 and 90 minutes following single dose lovastatin on Day 3.
Þ
Single-strength: one can of frozen concentrate diluted with 3 cans of water. Grapefruit juice was administered with breakfast for 3 days, and lovastatin was administered in the evening on Day 3.
ß
Cyclosporine-treated patients with psoriasis or post kidney or heart transplant patients with stable graft function, transplanted at least 9 months prior to study.
à
ND = Analyte not determined.
è
Lactone converted to acid by hydrolysis prior to analysis. Figure represents total unmetabolized acid and lactone.

Number of Subjects

Dosing of Co-Administered Drug or Grapefruit Juice

Dosing of Lovastatin

AUC Ratio* (with/without co-administered drug)

No Effect = 1.00

Lovastatin

Lovastatin Acid†

Gemfibrozil

11

600 mg BID for 3 days

40 mg

0.96

2.80

Itraconazole‡

12

200 mg QD for 4 days

40 mg on Day 4

>36§

22

10

100 mg QD for 4 days

40 mg on Day 4

>14.8§

15.4

Grapefruit Juice¶ (high dose)

10

200 mL of double-strength TID#

80 mg single dose

15.3

5.0

Grapefruit Juice¶ (low dose)

16

8 oz (about 250 mL) of single-strengthÞ for 4 days

40 mg single dose

1.94

1.57

Cyclosporine

16

Not describedß

10 mg QD for 10 days

5- to 8-fold

NDà

Number of Subjects

Dosing of Co-Administered Drug or Grapefruit Juice

Dosing of Lovastatin

AUC Ratio* (with/without co-administered drug)

No Effect = 1.00

Total Lovastatin Acidè

Diltiazem

10

120 mg BID for 14 days

20 mg

3.57è

___________________________________________________________________________

1Kantola, T, et al., Clin Pharmacol Ther 1998; 63(4):397-402.

CLINICAL PHARMACOLOGY II

Clinical Studies in Adults

Lovastatin has been shown to reduce total-C and LDL-C in heterozygous familial and non-familial forms of primary hypercholesterolemia and in mixed hyperlipidemia. A marked response was seen within 2 weeks, and the maximum therapeutic response occurred within 4 to 6 weeks. The response was maintained during continuation of therapy. Single daily doses given in the evening were more effective than the same dose given in the morning, perhaps because cholesterol is synthesized mainly at night.

In multicenter, double-blind studies in patients with familial or non-familial hypercholesterolemia, lovastatin, administered in doses ranging from 10 mg q.p.m. to 40 mg b.i.d., was compared to placebo. Lovastatin significantly decreased plasma total-C, LDL-C, total-C/HDL-C ratio and LDL-C/HDL-C ratio. In addition, lovastatin produced increases of variable magnitude in HDL-C, and modestly decreased VLDL-C and plasma TG (see Tables 2 through 4 for dose response results).

The results of a study in patients with primary hypercholesterolemia are presented in Table 2.

Table 2: Lovastatin vs. Placebo (Mean Percent Change from Baseline After 6 Weeks)

DOSAGE

N

TOTAL-C

LDL-C

HDL-C

LDL-C/
HDL-C

TOTAL-C
/HDL-C

TG

Placebo

33

-2

-1

-1

0

+1

+9

Lovastatin

10 mg q.p.m.

33

-16

-21

+5

-24

-19

-10

20 mg q.p.m.

33

-19

-27

+6

-30

-23

+9

10 mg b.i.d.

32

-19

-28

+8

-33

-25

-7

40 mg q.p.m.

33

-22

-31

+5

-33

-25

-8

20 mg b.i.d.

36

-24

-32

+2

-32

-24

-6

Lovastatin was compared to cholestyramine in a randomized open parallel study. The study was performed with patients with hypercholesterolemia who were at high risk of myocardial infarction. Summary results are presented in Table 3.

Table 3: Lovastatin vs. Cholestyramine (Percent Change from Baseline After 12 Weeks)

TREATMENT

N

TOTAL-C
(mean)

LDL-C
(mean)

HDL-C
(mean)

LDL-C
/HDL-C
(mean)

TOTAL-C/HDL-C
(mean)

VLDL-C
(median)

TG
(mean)

Lovastatin

20 mg b.i.d.

85

-27

-32

+9

-36

-31

-34

-21

40 mg b.i.d.

88

-34

-42

+8

-44

-37

-31

-27

Cholestyramine

12 g b.i.d.

88

-17

-23

+8

-27

-21

+2

+11

Lovastatin was studied in controlled trials in hypercholesterolemic patients with well-controlled non-insulin dependent diabetes mellitus with normal renal function. The effect of lovastatin on lipids and lipoproteins and the safety profile of lovastatin were similar to that demonstrated in studies in nondiabetics. Lovastatin had no clinically important effect on glycemic control or on the dose requirement of oral hypoglycemic agents.

Expanded Clinical Evaluation of Lovastatin [EXCEL] Study

Lovastatin was compared to placebo in 8,245 patients with hypercholesterolemia (total-C 240 mg/dL to 300 mg/dL [6.2 mmol/L to 7.6 mmol/L], LDL-C >160 mg/dL [4.1 mmol/L]) in the randomized, double-blind, parallel, 48-week EXCEL study. All changes in the lipid measurements (Table 4) in lovastatin treated patients were dose-related and significantly different from placebo (p<0.001). These results were sustained throughout the study.

Table 4: Lovastatin vs. Placebo (Percent Change from Baseline-Average Values Between Weeks 12 and 48)

*
Patients enrolled

DOSAGE

N*

TOTAL-C
(mean)

LDL-C
(mean)

HDL-C
(mean)

LDL-C/
HDL-C
(mean)

TOTAL-C/HDL-C
(mean)

TG
(median)

Placebo

1663

+0.7

+0.4

+2.0

+0.2

+0.6

+4

Lovastatin

20 mg q.p.m.

1642

-17

-24

+6.6

-27

-21

-10

40 mg q.p.m.

1645

-22

-30

+7.2

-34

-26

-14

20 mg b.i.d.

1646

-24

-34

+8.6

-38

-29

-16

40 mg b.i.d.

1649

-29

-40

+9.5

-44

-34

-19

CLINICAL PHARMACOLOGY III

Air Force/Texas Coronary Atherosclerosis Prevention Study (AFCAPS/TexCAPS)

The Air Force/Texas Coronary Atherosclerosis Prevention Study (AFCAPS/TexCAPS), a double-blind, randomized, placebo-controlled, primary prevention study, demonstrated that treatment with lovastatin decreased the rate of acute major coronary events (composite endpoint of myocardial infarction, unstable angina, and sudden cardiac death) compared with placebo during a median of 5.1 years of follow-up. Participants were middle-aged and elderly men (ages 45 to 73) and women (ages 55 to 73) without symptomatic cardiovascular disease with average to moderately elevated total-C and LDL-C, below average HDL-C, and who were at high risk based on elevated total-C/HDL-C. In addition to age, 63% of the participants had at least one other risk factor (baseline HDL-C <35 mg/dL, hypertension, family history, smoking and diabetes).

AFCAPS/TexCAPS enrolled 6,605 participants (5,608 men, 997 women) based on the following lipid entry criteria: total-C range of 180 mg/dL to 264 mg/dL, LDL-C range of 130 mg/dL to 190 mg/dL, HDL-C of <45 mg/dL for men and <47 mg/dL for women, and TG of <400 mg/dL. Participants were treated with standard care, including diet, and either lovastatin 20 mg to 40 mg daily (n=3,304) or placebo (n=3,301). Approximately 50% of the participants treated with lovastatin were titrated to 40 mg daily when their LDL-C remained >110 mg/dL at the 20 mg starting dose.

Lovastatin reduced the risk of a first acute major coronary event, the primary efficacy endpoint, by 37% (lovastatin 3.5%, placebo 5.5%; p<0.001; Figure 1). A first acute major coronary event was defined as myocardial infarction (54 participants on lovastatin, 94 on placebo) or unstable angina (54 vs. 80) or sudden cardiac death (8 vs. 9). Furthermore, among the secondary endpoints, lovastatin reduced the risk of unstable angina by 32% (1.8% vs. 2.6%; p=0.023), of myocardial infarction by 40% (1.7% vs. 2.9%; p=0.002), and of undergoing coronary revascularization procedures (e.g., coronary artery bypass grafting or percutaneous transluminal coronary angioplasty) by 33% (3.2% vs. 4.8%; p=0.001). Trends in risk reduction associated with treatment with lovastatin were consistent across men and women, smokers and non-smokers, hypertensives and non-hypertensives, and older and younger participants. Participants with >2 risk factors had risk reductions (RR) in both acute major coronary events (RR 43%) and coronary revascularization procedures (RR 37%). Because there were too few events among those participants with age as their only risk factor in this study, the effect of lovastatin on outcomes could not be adequately assessed in this subgroup.

[Figure 1]

Figure 1: Acute Major Coronary Events (Primary Endpoint)

Atherosclerosis

In the Canadian Coronary Atherosclerosis Intervention Trial (CCAIT), the effect of therapy with lovastatin on coronary atherosclerosis was assessed by coronary angiography in hyperlipidemic patients. In the randomized, double-blind, controlled clinical trial, patients were treated with conventional measures (usually diet and 325 mg of aspirin every other day) and either lovastatin 20 mg to 80 mg daily or placebo. Angiograms were evaluated at baseline and at two years by computerized quantitative coronary angiography (QCA). Lovastatin significantly slowed the progression of lesions as measured by the mean change per-patient in minimum lumen diameter (the primary endpoint) and percent diameter stenosis, and decreased the proportions of patients categorized with disease progression (33% vs. 50%) and with new lesions (16% vs. 32%).

In a similarly designed trial, the Monitored Atherosclerosis Regression Study (MARS), patients were treated with diet and either lovastatin 80 mg daily or placebo. No statistically significant difference between lovastatin and placebo was seen for the primary endpoint (mean change per patient in percent diameter stenosis of all lesions), or for most secondary QCA endpoints. Visual assessment by angiographers who formed a consensus opinion of overall angiographic change (Global Change Score) was also a secondary endpoint. By this endpoint, significant slowing of disease was seen, with regression in 23% of patients treated with lovastatin compared to 11% of placebo patients.

In the Familial Atherosclerosis Treatment Study (FATS), either lovastatin or niacin in combination with a bile acid sequestrant for 2.5 years in hyperlipidemic subjects significantly reduced the frequency of progression and increased the frequency of regression of coronary atherosclerotic lesions by QCA compared to diet and, in some cases, low-dose resin.

The effect of lovastatin on the progression of atherosclerosis in the coronary arteries has been corroborated by similar findings in another vasculature. In the Asymptomatic Carotid Artery Progression Study (ACAPS), the effect of therapy with lovastatin on carotid atherosclerosis was assessed by B-mode ultrasonography in hyperlipidemic patients with early carotid lesions and without known coronary heart disease at baseline. In this double-blind, controlled clinical trial, 919 patients were randomized in a 2 x 2 factorial design to placebo, lovastatin 10 mg to 40 mg daily and/or warfarin. Ultrasonograms of the carotid walls were used to determine the change per patient from baseline to three years in mean maximum intimal-medial thickness (IMT) of 12 measured segments. There was a significant regression of carotid lesions in patients receiving lovastatin alone compared to those receiving placebo alone (p=0.001). The predictive value of changes in IMT for stroke has not yet been established. In the lovastatin group there was a significant reduction in the number of patients with major cardiovascular events relative to the placebo group (5 vs. 14) and a significant reduction in all-cause mortality (1 vs. 8).

Eye

There was a high prevalence of baseline lenticular opacities in the patient population included in the early clinical trials with lovastatin. During these trials the appearance of new opacities was noted in both the lovastatin and placebo groups. There was no clinically significant change in visual acuity in the patients who had new opacities reported nor was any patient, including those with opacities noted at baseline, discontinued from therapy because of a decrease in visual acuity.

A three-year, double-blind, placebo-controlled study in hypercholesterolemic patients to assess the effect of lovastatin on the human lens demonstrated that there were no clinically or statistically significant differences between the lovastatin and placebo groups in the incidence, type or progression of lenticular opacities. There are no controlled clinical data assessing the lens available for treatment beyond three years.

Clinical Studies in Adolescent Patients

Efficacy of Lovastatin in Adolescent Boys with Heterozygous Familial Hypercholesterolemia

In a double-blind, placebo-controlled study, 132 boys 10 to 17 years of age (mean age 12.7 yrs) with heterozygous familial hypercholesterolemia (heFH) were randomized to lovastatin (n=67) or placebo (n=65) for 48 weeks. Inclusion in the study required a baseline LDL-C level between 189 mg/dL and 500 mg/dL and at least one parent with an LDL-C level > 189 mg/dL. The mean baseline LDL-C value was 253.1 mg/dL (range: 171 mg/dL to 379 mg/dL) in the lovastatin group compared to 248.2 mg/dL (range: 158.5 mg/dL to 413.5 mg/dL) in the placebo group. The dosage of lovastatin (once daily in the evening) was 10 mg for the first 8 weeks, 20 mg for the second 8 weeks, and 40 mg thereafter.

Lovastatin significantly decreased plasma levels of total-C, LDL-C and apolipoprotein B (see Table 5).

Table 5: Lipid-lowering Effects of Lovastatin in Adolescent Boys with Heterozygous Familial Hypercholesterolemia (Mean Percent Change from Baseline at Week 48 in Intention-to-Treat Population)

*
data presented as median percent changes

DOSAGE

N

TOTAL-C

LDL-C

HDL-C

TG*

Apolipoprotein B

Placebo

61

-1.1

-1.4

-2.2

-1.4

-4.4

Lovastatin

64

-19.3

-24.2

+1.1

-1.9

-21

The mean achieved LDL-C value was 190.9 mg/dL (range: 108 mg/dL to 336 mg/dL) in the lovastatin group compared to 244.8 mg/dL (range: 135 mg/dL to 404 mg/dL) in the placebo group.

Efficacy of Lovastatin in Post-Menarchal Girls with Heterozygous Familial Hypercholesterolemia

In a double-blind, placebo-controlled study, 54 girls 10 to 17 years of age who were at least 1 year post-menarche with heFH were randomized to lovastatin (n=35) or placebo (n=19) for 24 weeks. Inclusion in the study required a baseline LDL-C level of 160 mg/dL to 400 mg/dL and a parental history of familial hypercholesterolemia. The mean baseline LDL-C value was 218.3 mg/dL (range: 136.3 mg/dL to 363.7 mg/dL) in the lovastatin group compared to 198.8 mg/dL (range: 151.1 mg/dL to 283.1 mg/dL) in the placebo group. The dosage of lovastatin (once daily in the evening) was 20 mg for the first 4 weeks, and 40 mg thereafter.

Lovastatin significantly decreased plasma levels of total-C, LDL-C, and apolipoprotein B (see Table 6).

Table 6: Lipid-lowering Effects of Lovastatin in Post-Menarchal Girls with Heterozygous Familial Hypercholesterolemia (Mean Percent Change from Baseline at Week 24 in Intention-to-Treat Population)

*
data presented as median percent changes

DOSAGE

N

TOTAL-C

LDL-C

HDL-C

TG*

Apolipoprotein B

Placebo

18

+3.6

+2.5

+4.8

-3.0

+6.4

Lovastatin

35

-22.4

-29.2

+2.4

-22.7

-24.4

The mean achieved LDL-C value was 154.5 mg/dL (range: 82 mg/dL to 286 mg/dL) in the lovastatin group compared to 203.5 mg/dL (range: 135 mg/dL to 304 mg/dL) in the placebo group.

The safety and efficacy of doses above 40 mg daily have not been studied in children. The long-term efficacy of lovastatin therapy in childhood to reduce morbidity and mortality in adulthood has not been established.

INDICATIONS AND USAGE

Therapy with lovastatin tablets USP should be a component of multiple risk factor intervention in those individuals with dyslipidemia at risk for atherosclerotic vascular disease. Lovastatin tablets USP should be used in addition to a diet restricted in saturated fat and cholesterol as part of a treatment strategy to lower total-C and LDL-C to target levels when the response to diet and other nonpharmacological measures alone has been inadequate to reduce risk.

Primary Prevention of Coronary Heart Disease

In individuals without symptomatic cardiovascular disease, average to moderately elevated total-C and LDL-C, and below average HDL-C, lovastatin tablets USP are indicated to reduce the risk of:

- Myocardial infarction

- Unstable angina

- Coronary revascularization procedures

(See CLINICAL PHARMACOLOGY, Clinical Studies)

Coronary Heart Disease

Lovastatin tablets USP are indicated to slow the progression of coronary atherosclerosis in patients with coronary heart disease as part of a treatment strategy to lower total-C and LDL-C to target levels.

Hypercholesterolemia

Therapy with lipid-altering agents should be a component of multiple risk factor intervention in those individuals at significantly increased risk for atherosclerotic vascular disease due to hypercholesterolemia. Lovastatin tablets USP are indicated as an adjunct to diet for the reduction of elevated total-C and LDL-C levels in patients with primary hypercholesterolemia (Types IIa and IIb2), when the response to diet restricted in saturated fat and cholesterol and to other nonpharmacological measures alone has been inadequate.

____________________________________________________

2Classification of Hyperlipoproteinemias

Lipid Elevations

Type

Lipoproteins Elevated

Major

Minor

I

chylomicrons

TG

↑→C

IIa

LDL

C

−

IIb

LDL, VLDL

C

TG

III (rare)

IDL

C/TG

−

IV

VLDL

TG

↑→C

V (rare)

chylomicrons, VLDL

TG

↑→C

IDL = intermediate-density lipoprotein.

Adolescent Patients with Heterozygous Familial Hypercholesterolemia

Lovastatin tablets USP are indicated as an adjunct to diet to reduce total-C, LDL-C and apolipoprotein B levels in adolescent boys and girls who are at least one year post-menarche, 10 to 17 years of age, with heFH if after an adequate trial of diet therapy the following findings are present:

1. LDL-C remains >189 mg/dL or

2. LDL-C remains >160 mg/dL and:

•there is a positive family history of premature cardiovascular disease or

•
two or more other CVD risk factors are present in the adolescent patients
General Recommendations

Prior to initiating therapy with lovastatin tablets USP, secondary causes for hypercholesterolemia (e.g., poorly controlled diabetes mellitus, hypothyroidism, nephrotic syndrome, dysproteinemias, obstructive liver disease, other drug therapy, alcoholism) should be excluded, and a lipid profile performed to measure total-C, HDL-C, and TG. For patients with TG less than 400 mg/dL (<4.5 mmol/L), LDL-C can be estimated using the following equation:

LDL-C = total-C - [0.2 x (TG) + HDL-C]

For TG levels >400 mg/dL (>4.5 mmol/L), this equation is less accurate and LDL-C concentrations should be determined by ultracentrifugation. In hypertriglyceridemic patients, LDL-C may be low or normal despite elevated total-C. In such cases, lovastatin tablets USP are not indicated.

The National Cholesterol Education Program (NCEP) Treatment Guidelines are summarized below:

CHD, coronary heart disease
Some authorities recommend use of LDL-lowering drugs in this category if an LDL-C level of <100 mg/dL cannot be achieved by therapeutic lifestyle changes. Others prefer use of drugs that primarily modify triglycerides and HDL-C, e.g., nicotinic acid or fibrate. Clinical judgment also may call for deferring drug therapy in this subcategory.
Almost all people with 0-1 risk factor have a 10-year risk <10%; thus, 10-year risk assessment in people with 0-1 risk factor is not necessary.

NCEP Treatment Guidelines: LDL-C Goals and Cutpoints for Therapeutic Lifestyle Changes and Drug Therapy in Different Risk Categories

Risk Category

LDL Goal
(mg/dL)

LDL Level at Which to Initiate Therapeutic Lifestyle Changes
(mg/dL)

LDL Level at Which to Consider Drug Therapy
(mg/dL)

CHD*or CHD risk equivalents
(10-year risk >20%)

<100

≥100

≥130
(100-129: drug optional)†

2+ Risk factors
(10-year risk ≤20%)

<130

≥130

10-year risk 10-20%: ≥130
10-year risk <10%: ≥160

0-1 Risk factor

<160

≥160

≥190
(160-189: LDL-lowering drug optional)

After the LDL-C goal has been achieved, if the TG is still >200 mg/dL, non HDL-C (total-C minus HDL-C) becomes a secondary target of therapy. Non-HDL-C goals are set 30 mg/dL higher than LDL-C goals for each risk category.

At the time of hospitalization for an acute coronary event, consideration can be given to initiating drug therapy at discharge if the LDL-C is >130 mg/dL (see NCEP Guidelines above).

Since the goal of treatment is to lower LDL-C, the NCEP recommends that LDL-C levels be used to initiate and assess treatment response. Only if LDL-C levels are not available, should the total-C be used to monitor therapy.

Although lovastatin tablets USP may be useful to reduce elevated LDL-C levels in patients with combined hypercholesterolemia and hypertriglyceridemia where hypercholesterolemia is the major abnormality (Type IIb hyperlipoproteinemia), it has not been studied in conditions where the major abnormality is elevation of chylomicrons, VLDL or IDL (i.e., hyperlipoproteinemia types I, III, IV, or V).2

2 Classification of Hyperlipoproteinemias

The NCEP classification of cholesterol levels in pediatric patients with a familial history of hypercholesterolemia or premature cardiovascular disease is summarized below:

Category

Total-C (mg/dL)

LDL-C (mg/dL)

Acceptable

<170

<110

Borderline

170 to 199

110 to 129

High

≥200

≥130

CONTRAINDICATIONS

Hypersensitivity to any component of this medication.

Active liver disease or unexplained persistent elevations of serum transaminases (see WARNINGS).

Concomitant administration with strong CYP3A4 inhibitors (e.g., itraconazole, ketoconazole, posaconazole, voriconazole, HIV protease inhibitors, boceprevir, telaprevir, erythromycin, clarithromycin, telithromycin, nefazodone, and cobicistat-containing products) (see WARNINGS, Myopathy/Rhabdomyolysis).

Pregnancy and Lactation

(See PRECAUTIONS, Pregnancy and Nursing Mothers).

Atherosclerosis is a chronic process and the discontinuation of lipid-lowering drugs during pregnancy should have little impact on the outcome of long-term therapy of primary hypercholesterolemia. Moreover, cholesterol and other products of the cholesterol biosynthesis pathway are essential components for fetal development, including synthesis of steroids and cell membranes. Because of the ability of inhibitors of HMG-CoA reductase such as lovastatin to decrease the synthesis of cholesterol and possibly other products of the cholesterol biosynthesis pathway, lovastatin is contraindicated during pregnancy and in nursing mothers. Lovastatin should be administered to women of childbearing age only when such patients are highly unlikely to conceive. If the patient becomes pregnant while taking this drug, lovastatin should be discontinued immediately and the patient should be apprised of the potential hazard to the fetus (see PRECAUTIONS, Pregnancy).

WARNINGS

Hypersensitivity to any component of this medication.

Active liver disease or unexplained persistent elevations of serum transaminases (see WARNINGS).

Concomitant administration with strong CYP3A4 inhibitors (e.g., itraconazole, ketoconazole, posaconazole, voriconazole, HIV protease inhibitors, boceprevir, telaprevir, erythromycin, clarithromycin, telithromycin, nefazodone, and cobicistat-containing products) (see WARNINGS, Myopathy/Rhabdomyolysis).

Pregnancy and Lactation

(See PRECAUTIONS, Pregnancy and Nursing Mothers).

Atherosclerosis is a chronic process and the discontinuation of lipid-lowering drugs during pregnancy should have little impact on the outcome of long-term therapy of primary hypercholesterolemia. Moreover, cholesterol and other products of the cholesterol biosynthesis pathway are essential components for fetal development, including synthesis of steroids and cell membranes. Because of the ability of inhibitors of HMG-CoA reductase such as lovastatin to decrease the synthesis of cholesterol and possibly other products of the cholesterol biosynthesis pathway, lovastatin is contraindicated during pregnancy and in nursing mothers. Lovastatin should be administered to women of childbearing age only when such patients are highly unlikely to conceive. If the patient becomes pregnant while taking this drug, lovastatin should be discontinued immediately and the patient should be apprised of the potential hazard to the fetus (see PRECAUTIONS, Pregnancy).